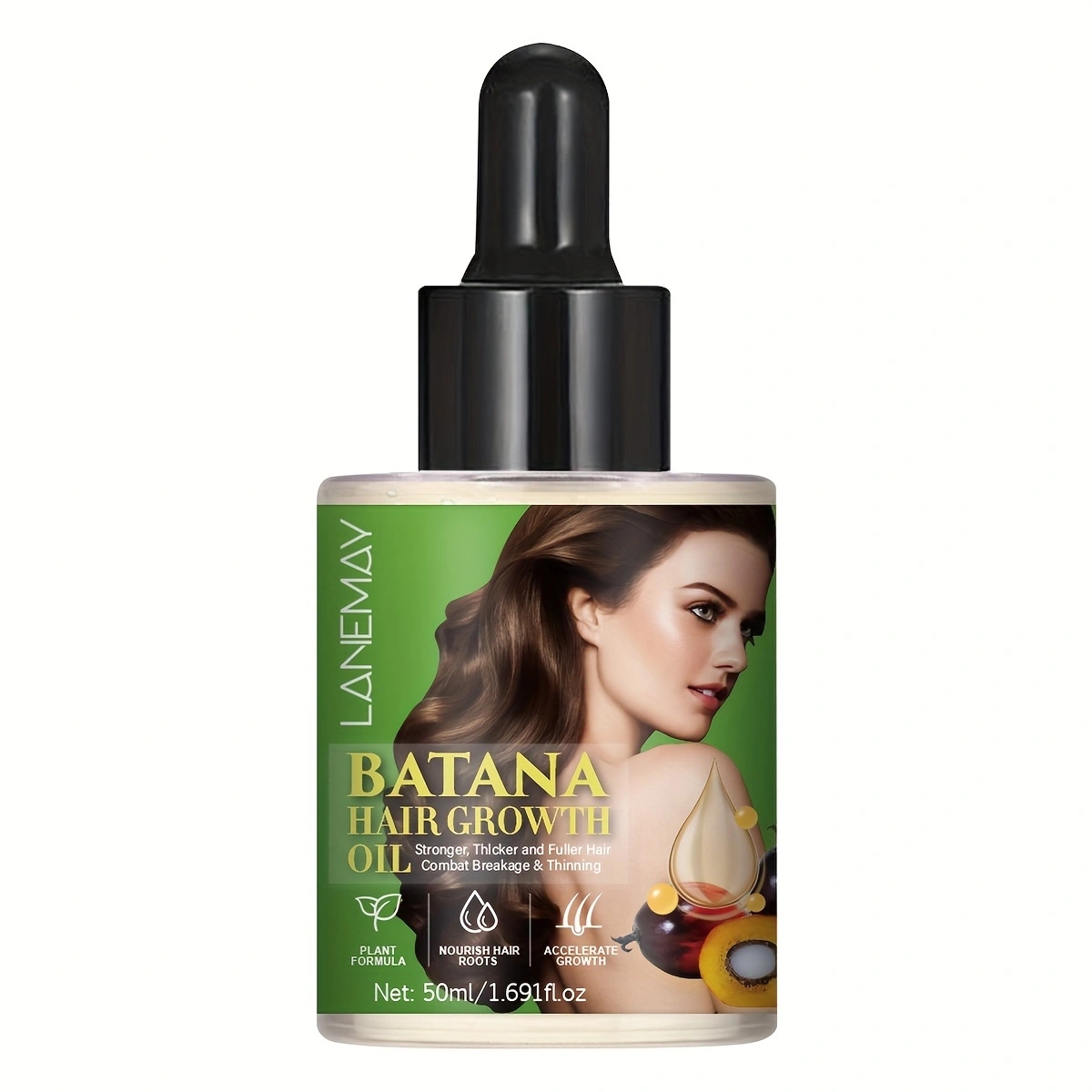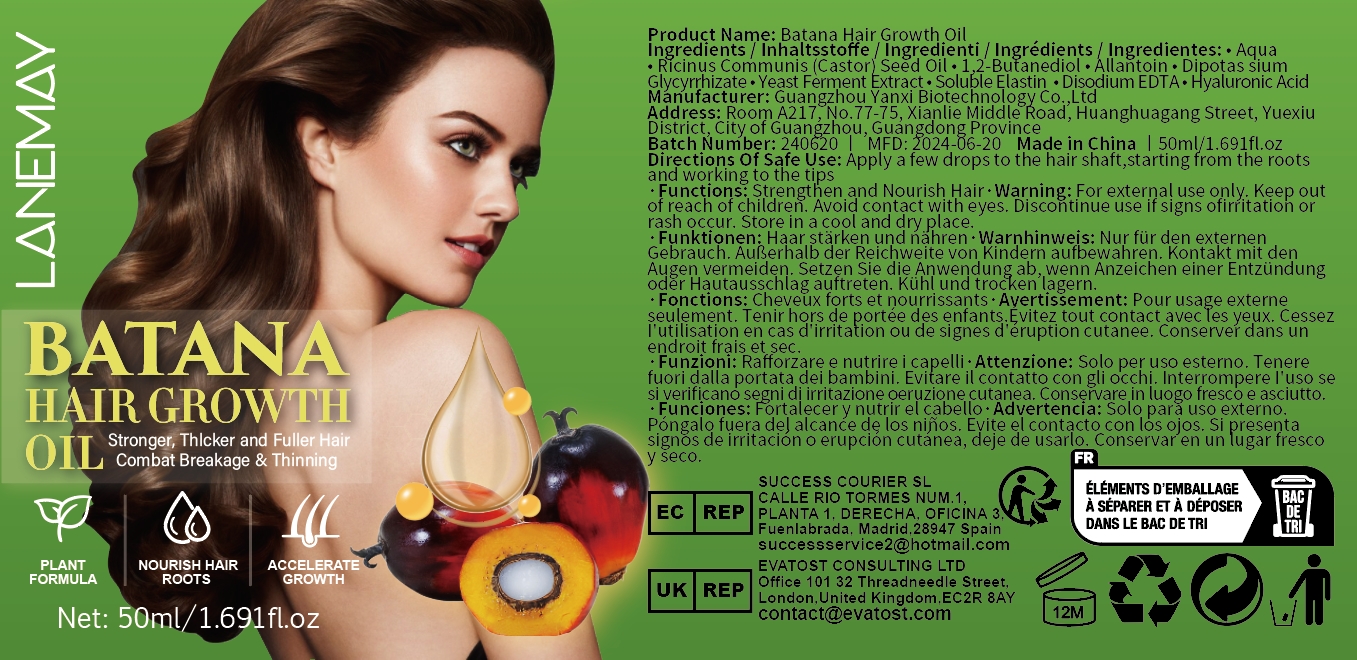 DRUG LABEL: Batana Hair GrowthOil
NDC: 84025-074 | Form: OIL
Manufacturer: Guangzhou Yanxi Biotechnology Co..Ltd
Category: otc | Type: HUMAN OTC DRUG LABEL
Date: 20240720

ACTIVE INGREDIENTS: 1,2-BUTANEDIOL 5 mg/50 mL; ALLANTOIN 3 mg/50 mL
INACTIVE INGREDIENTS: WATER

DOSAGE AND ADMINISTRATION

Nourish hair

WARNINGS

Keep out of children

INACTIVE INGREDIENT

Aqua

INDICATIONS AND USAGE

Treatment of dry and rough hair

keep out of children

PURPOSE

Nourishes scalp and hair